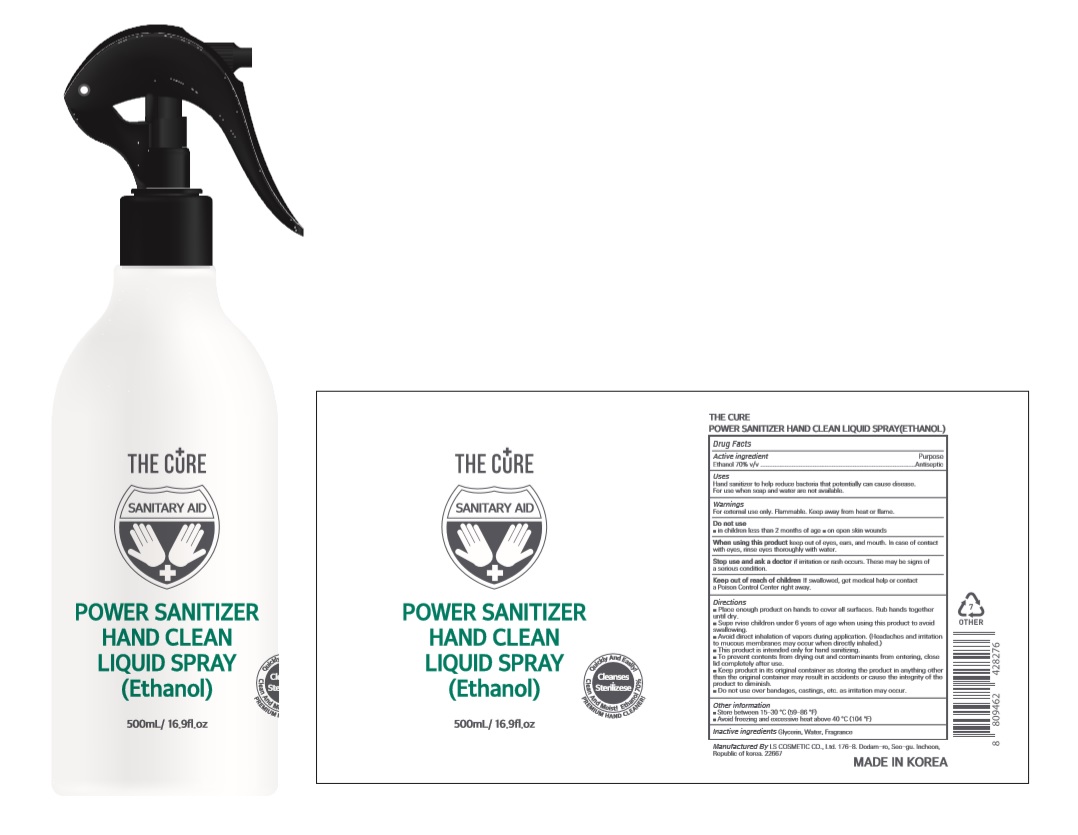 DRUG LABEL: THE CURE POWER SANITIZER HAND CLEAN LIQUIDSpray(Ethanol)
NDC: 59545-1570 | Form: SPRAY
Manufacturer: LS COSMETIC CO.,LTD.
Category: otc | Type: HUMAN OTC DRUG LABEL
Date: 20200614

ACTIVE INGREDIENTS: ALCOHOL 350 mL/500 mL
INACTIVE INGREDIENTS: GLYCERIN; WATER

THE CURE POWER SANITIZER HAND CLEAN LIQUID SPRAY(Ethanol) : 59545-1570-1 | 500 mL | Bottle+Spray